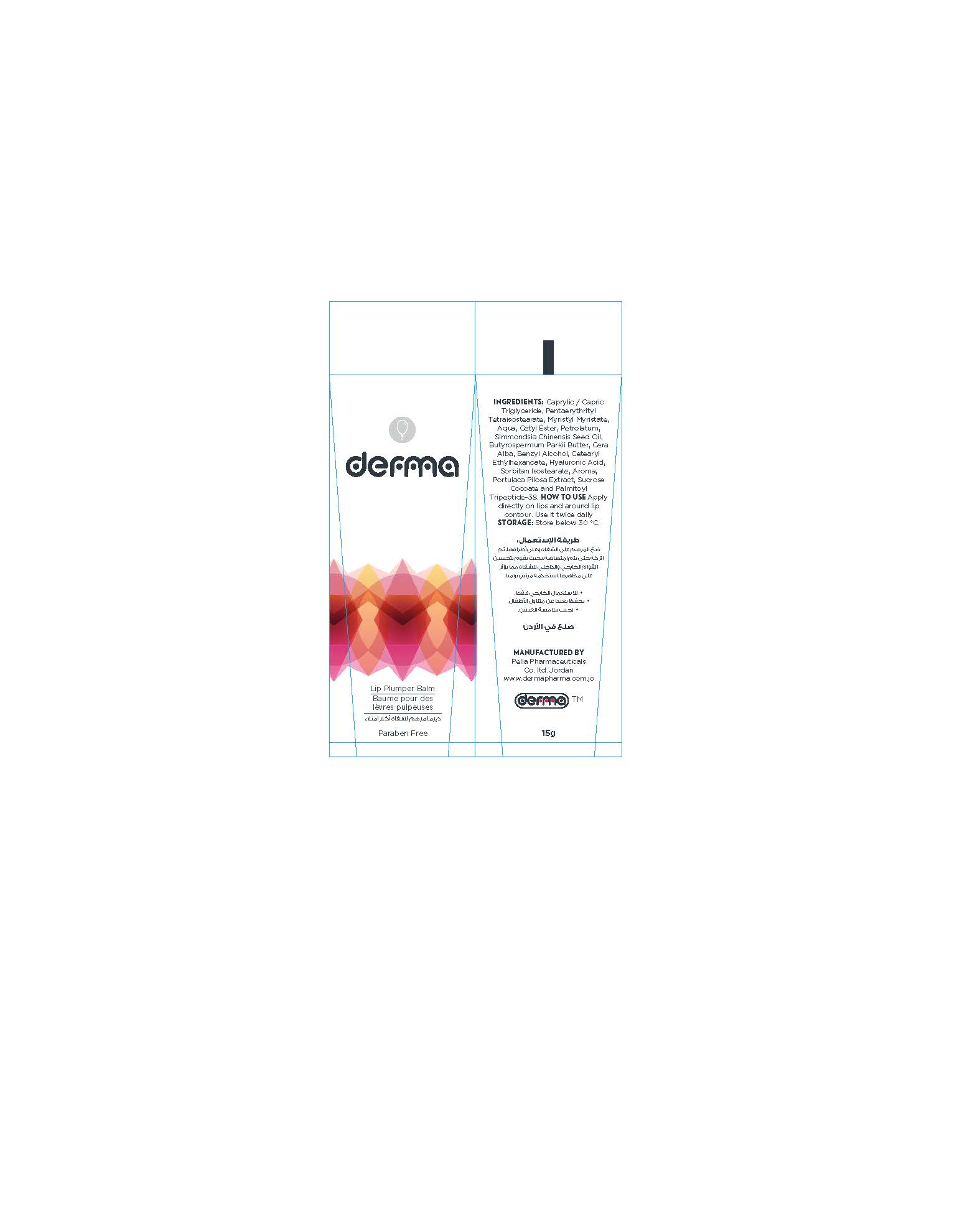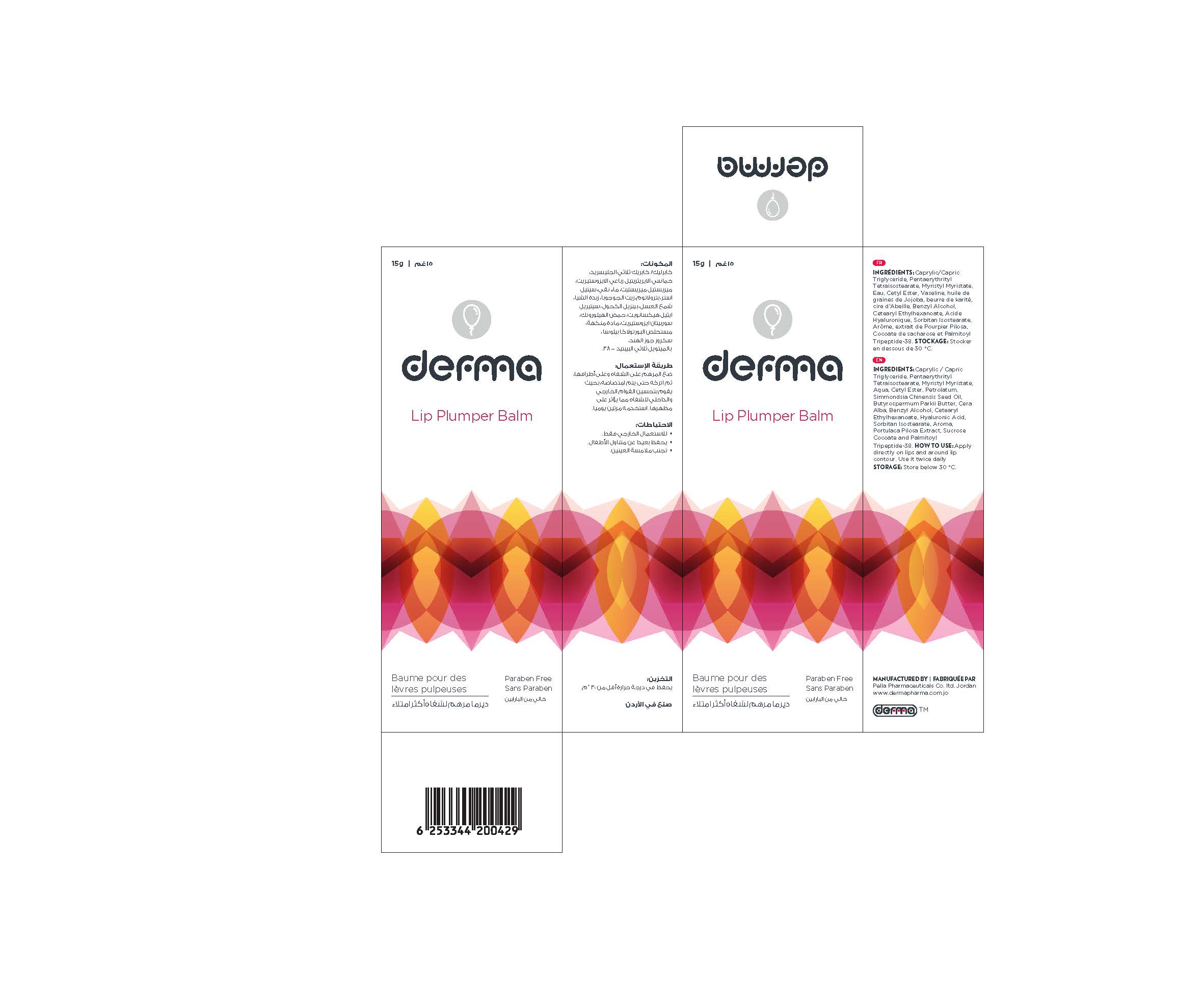 DRUG LABEL: Derma Lip Plumper Balm
NDC: 82160-429 | Form: LIPSTICK
Manufacturer: Pella Pharmaceuticals Co. ltd
Category: otc | Type: HUMAN OTC DRUG LABEL
Date: 20211129

ACTIVE INGREDIENTS: PALMITOYL LYSYLDIOXYMETHIONYLLYSINE 0.00075 mg/15 g; PORTULACA PILOSA WHOLE 0.03 mg/15 g; HYALURONIC ACID 0.15 mg/15 g
INACTIVE INGREDIENTS: WATER; PETROLATUM; JOJOBA OIL; SORBITAN ISOSTEARATE; SHEA BUTTER; BENZYL ALCOHOL; CETEARYL ETHYLHEXANOATE; SUCROSE COCOATE; MEDIUM-CHAIN TRIGLYCERIDES; PENTAERYTHRITYL TETRAISOSTEARATE; MYRISTYL MYRISTATE; WHITE WAX; CETYL ESTERS WAX; POTASSIUM SORBATE

Lip Plumper

Forms and presentation

Balm: Tube of 15 g.

Active Ingredints

Hyaluronic Acid

Portulaca Pilosa Extract

Palmitoyl Tripeptide-38

Inactive ingredients

Caprylic / Capric Triglyceride, Pentaerytbrityl Tetraisostearate, Myristyl Myristate, Aqua, Cetyl Ester, Petrolatum, Simmondsia Chinensis Seed Oil, Butyrospermum Parkii Butter, Cera Alba, Benzyl Alcohol, Cetearyl Ethylhexanoate, Sorbitan Isostearate, Aroma and Sucrose Cocoate

Purpose

Lip plumper

Properties

Lip balm has a unique formula that lets the lips look full and moist naturally, and it reduces the cracks.
Paraben free.

Indications

Lip plumper balm

Precaution

Keep out of reach of children

Warnings

- For external use only
- Avoid contact with eyes

Contraindications

Hypersensitivity to any of the components.

Side effects

There are no known side effects.

Dosage and administration

Apply directly on lips and around lip contour. Use it twice daily

Storage conditions

Store at a temperature below 30 °C.